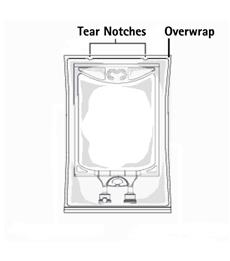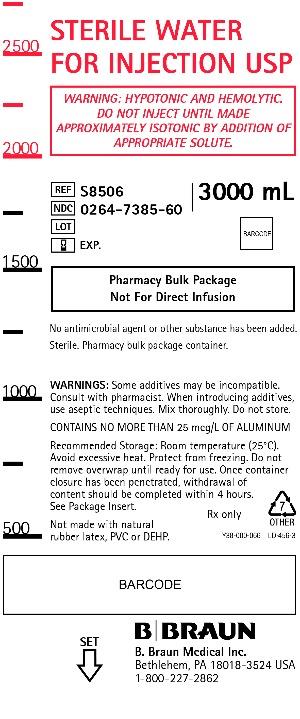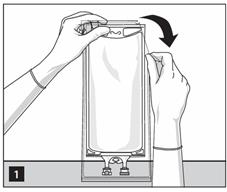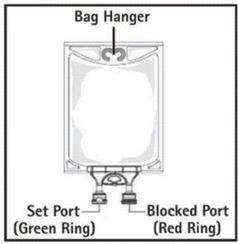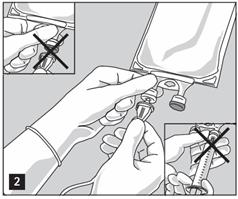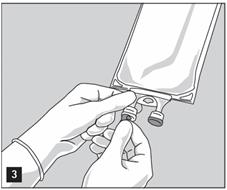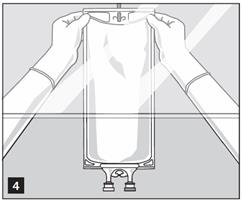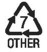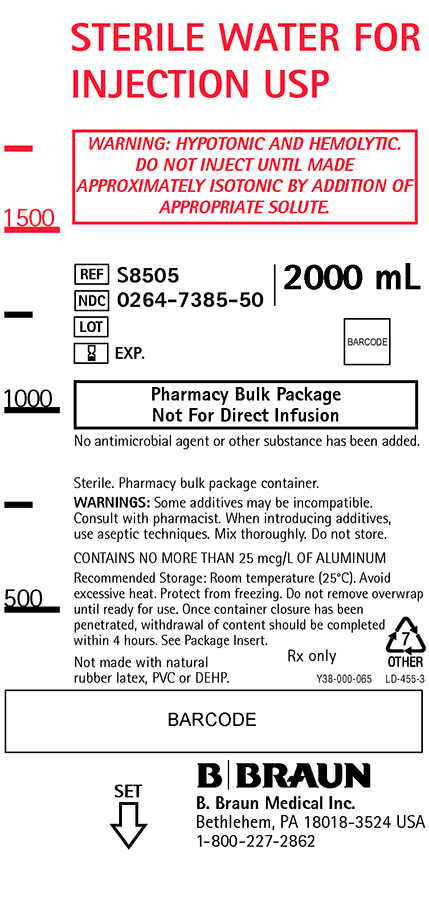 DRUG LABEL: Sterile Water
NDC: 0264-7385 | Form: INJECTION
Manufacturer: B. Braun Medical Inc.
Category: prescription | Type: HUMAN PRESCRIPTION DRUG LABEL
Date: 20210806

ACTIVE INGREDIENTS: WATER 1 mL/1 mL

Sterile Water for Injection USP

Warning: Hypotonic and hemolytic.
Do not inject until made approximately isotonic by addition of appropriate solute.

Pharmacy Bulk Package
Not For Direct Infusion

DESCRIPTION

Sterile Water for Injection USP is a clear, colorless, odorless liquid. It is sterile, hypotonic, nonpyrogenic, and contains no bacteriostatic or antimicrobial agents. Sterile Water for Injection USP is a diluent suitable for intravascular injection after first having been made approximately isotonic by the addition of suitable solute.

pH: 5.5 (5.0-7.0)

Not made with natural rubber latex, PVC or DEHP.

The plastic container is made from a multilayered film specifically developed for parenteral drugs. It contains no plasticizers and exhibits virtually no leachables. The solution contact layer is a rubberized copolymer of ethylene and propylene. The container is nontoxic and biologically inert. The container-solution unit is a closed system and is not dependent upon entry of external air during use. The container is overwrapped to provide protection from the physical environment and to provide an additional moisture barrier when necessary.

CLINICAL PHARMACOLOGY

Sterile Water for Injection USP is used as a diluent for other parenteral drugs. As such, Sterile Water for Injection USP contributes to the water for hydration when provided in parenteral drug and fluid therapy, after the introduction of suitable additives and/or mixture with suitable solutes to approximate isotonicity.

INDICATIONS AND USAGE

Sterile Water for Injection USP is indicated for use in adults and pediatric patients as a diluent in the aseptic preparation of parenteral solutions or as a vehicle for drug administration after admixture or dilution.

CONTRAINDICATIONS

None known.

WARNINGS

This solution is for compounding only, not for direct infusion.

Hypotonic and hemolytic. Do not inject until made approximately isotonic by addition of an appropriate solute, due to the possibility of hemolysis.

The administration of intravenous solutions can cause fluid and/or solute overload resulting in dilution of serum electrolyte concentrations, overhydration, congested states or pulmonary edema. The risk of dilutional states is inversely proportional to the electrolyte concentration.

WARNING: This product contains aluminum that may be toxic. Aluminum may reach toxic levels with prolonged parenteral administration if kidney function is impaired. Premature neonates are particularly at risk because their kidneys are immature, and they require large amounts of calcium and phosphate solutions, which contain aluminum.

Research indicates that patients with impaired kidney function, including premature neonates, who receive parenteral levels of aluminum at greater than 4 to 5 mcg/kg/day accumulate aluminum at levels associated with central nervous system and bone toxicity. Tissue loading may occur at even lower rates of administration.

PRECAUTIONS

General

To minimize the risk of possible incompatibilities arising from the mixing of additives that may be prescribed, the final infusate should be inspected for cloudiness or precipitation immediately after mixing, prior to administration and periodically during administration.

Do not use plastic container in series connection.

If administration of Sterile Water for Injection USP after admixture or dilution is controlled by a pumping device, care must be taken to discontinue pumping action before the container runs dry or air embolism may result. If administration is not controlled by a pumping device, refrain from applying excessive pressure (>300mmHg) causing distortion to the container such as wringing or twisting. Such handling could result in breakage of the container.

This solution is intended for intravenous administration after admixture or dilution using sterile equipment. It is recommended that intravenous administration apparatus be replaced at least once every 24 hours.

Use only if solution is clear and container and seals are intact.

The drug product contains no more than 25 mcg/L of aluminum.

Carcinogenesis, Mutagenesis, Impairment of Fertility

Refer to the package insert of the solute used.

Usage in Pregnancy

Refer to the package insert of the solute used.

Nursing Mothers

Refer to the package insert of the solute used.

Pediatric Use

Refer to the package insert of the solute used. See WARNINGS section regarding aluminum.

Geriatric Use

Refer to the package insert of the solute used. See WARNINGS section regarding aluminum.

ADVERSE REACTIONS

Refer to the package insert of the solute used.

Reactions which may occur because of the solution or the technique of administration include febrile response, infection at the site of injection, venous thrombosis or phlebitis extending from the site of injection, extravasation and hypervolemia.

The physician should also be alert to the possibility of adverse reactions to drug additives. Prescribing information for drug additives to be administered in this manner should be consulted.

If an adverse reaction does occur, discontinue the infusion, evaluate the patient, institute appropriate therapeutic countermeasures and save the remainder of the fluid for examination if deemed necessary.

OVERDOSAGE

Overdosage (hypotonic expansion) is a function of an increase in fluid intake over fluid output, and occurs when the increase in the volume of body fluids is due to water alone. Overdosage may occur in patients who receive large quantities of electrolyte-free water to replace abnormal excessive fluid losses, in patients whose renal tolerance to water loads is exceeded, or in patients who retain water postoperatively in response to stress.

Manifestations of water intoxication are behavioral changes (confusion, apathy, disorientation and attendant hyponatremia), central nervous system disturbances (weakness, muscle twitching, headaches, nausea, vomiting, convulsions) and weight gain.

Treatment consists of withholding fluids until excessive water is excreted. In severe hyponatremia it may be necessary to cautiously administer hypertonic saline to increase extracellular osmotic pressure and excretion of excess water by the kidneys.

DOSAGE AND ADMINISTRATION

This solution is for intravenous use only after admixture or dilution. Do not inject until made approximately isotonic by addition of appropriate solute.

Following suitable admixture of prescribed drugs, the dosage is usually dependent upon the age, weight and clinical condition of the patient as well as laboratory determinations. See directions accompanying drugs.

The dosage and administration of Sterile Water for Injection USP is dependent upon the recommended dosage and administration of the solute used. Fluid administration should be based on calculated maintenance or replacement fluid requirements for each patient.

Some additives may be incompatible. Consult with pharmacist. When performing admixture or dilution, use aseptic techniques. Mix thoroughly. Do not store.

Parenteral drug products should be inspected visually for particulate matter and discoloration prior to administration, whenever solution and container permit.

HOW SUPPLIED

Sterile Water for Injection USP is supplied in 2000 and 3000 mL Pharmacy Bulk Package containers packaged 4 per case.

NDC | REF | Size
0264-7385-50 | S8505 | 2000 mL
0264-7385-60 | S8506 | 3000 mL

STORAGE AND HANDLING

Exposure of pharmaceutical products to heat should be minimized. Avoid excessive heat. Protect from freezing. It is recommended that the product be stored at room temperature (25°C); however, brief exposure up to 40°C does not adversely affect the product.

Rx only

Revised: May 2019

Directions for use of Plastic Container

Warning: Hypotonic and hemolytic. Do not inject until made approximately isotonic by addition of appropriate solute.

Parenteral drug products should be inspected visually for particulate matter and discoloration prior to administration and final infusate should be inspected for cloudiness or precipitation immediately after mixing, prior to administration, and periodically during administration, whenever solution and container permit. Use of a final filter is recommended during administration of all parenteral solutions where possible.

Sterile Water for Injection USP in the Pharmacy Bulk Package is intended for use in the preparation of sterile, intravenous admixtures. Additives may be incompatible with the fluid withdrawn from this container. Complete information is not available. Those additives known to be incompatible should not be used. Consult with pharmacist, if available.

When compounding admixtures, use aseptic technique. Mix thoroughly.

Do not store any unused portion of Sterile Water for Injection USP.

Preparation

- Inspect overwrap and primary bag.
- Do not use if overwrap has been damaged.
- Do not use unless solution is clear and closure is intact.

1. To open: Tear overwrap starting from the tear notches. (Figure 1)

For Pharmacy Bulk Packages

- The Pharmacy Bulk Package is to be used only in a suitable work area such as a laminar air flow hood (or an equivalent clean air compounding area).
- For compounding only. Do not use for direct infusion.
- Do not use/penetrate blocked port (see Figure 2, left upper corner).
- Suspend container.
- Remove aluminum foil of set port at the bottom of container (see Figure 3).
- Attach suitable transfer device or compounding set (Figure 2). Refer to complete directions accompanying device.
- Hang bag on suitable fixture (Figure 4).
- Once container closure has been penetrated, withdrawal of content should be completed within 4 hours.

Important Admixing Instructions

- The contents are intended for use in a pharmacy admixture program and are restricted to the preparation of admixtures for infusion or, through a sterile transfer device, for the filling of empty sterile syringes.
- Additives may be incompatible with the fluid withdrawn from this container. Consult with pharmacist, if available. When compounding admixtures, use aseptic technique, mix thoroughly and do not store.
- Parenteral drug products should be inspected visually for particulate matter and discoloration prior to administration, whenever solution container permits. (See PRECAUTIONS, General).

B. Braun Medical Inc.
Bethlehem, PA 18018-3524 USA
1-800-227-2862
www.bbraun.com
Made in USA

Y36-002-998 LD-454-2

PRINCIPAL DISPLAY PANEL - 2000 mL

STERILE WATER FOR
INJECTION USP

WARNING: HYPOTONIC AND HEMOLYTIC.
DO NOT INJECT UNTIL MADE
APPROXIMATELY ISOTONIC BY ADDITION OF
APPROPRIATE SOLUTE.

REF S8505
NDC 0264-7385-50
LOT
EXP.

2000 mL

Pharmacy Bulk Package
Not For Direct Infusion

No antimicrobial agent or other substance has been added.

Sterile. Pharmacy bulk package container.

WARNINGS: Some additives may be incompatible.
Consult with pharmacist. When introducing additives,
use aseptic techniques. Mix thoroughly. Do not store.

CONTAINS NO MORE THAN 25 mcg/L OF ALUMINUM

Recommended Storage: Room temperature (25°C). Avoid
excessive heat. Protect from freezing. Do not remove overwrap
until ready for use. Once container closure has been
penetrated, withdrawal of content should be completed
within 4 hours. See Package Insert.

Not made with natural rubber latex, PVC or DEHP.

Rx only

Y38-000-065 LD-455-3

B. Braun Medical Inc.
Bethlehem, PA 18018-3524 USA
1-800-227-2862

SET

Sterile Water Injection 2L Container Label

PRINCIPAL DISPLAY PANEL - 3000 mL

STERILE WATER
FOR INJECTION USP

WARNING: HYPOTONIC AND HEMOLYTIC.
DO NOT INJECT UNTIL MADE
APPROXIMATELY ISOTONIC BY ADDITION OF
APPROPRIATE SOLUTE.

REF S8506
NDC 0264-7385-60
LOT
EXP.

3000 mL

Pharmacy Bulk Package
Not For Direct Infusion

No antimicrobial agent or other substance has been added.

Sterile. Pharmacy bulk package container.

WARNINGS: Some additives may be incompatible.
Consult with pharmacist. When introducing additives,
use aseptic techniques. Mix thoroughly. Do not store.

CONTAINS NO MORE THAN 25 mcg/L OF ALUMINUM

Recommended Storage: Room temperature (25°C).
Avoid excessive heat. Protect from freezing. Do not
remove overwrap until ready for use. Once container
closure has been penetrated, withdrawal of
content should be completed within 4 hours.
See Package Insert.

Not made with natural rubber latex, PVC or DEHP.

Rx only

Y38-000-066 LD-456-3

B. Braun Medical Inc.
Bethlehem, PA 18018-3524 USA
1-800-227-2862

SET